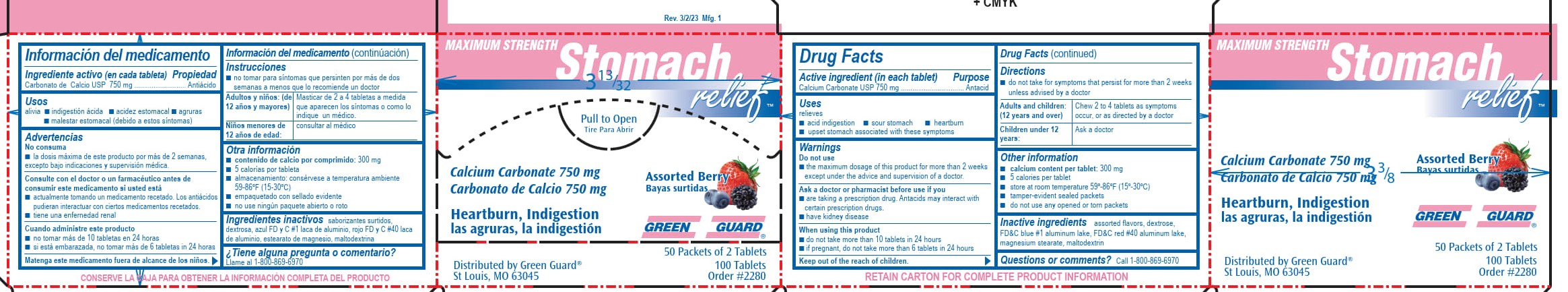 DRUG LABEL: Green Guard Maximum Strength Stomach Relief
NDC: 47682-850 | Form: TABLET, CHEWABLE
Manufacturer: Unifirst First Aid Corporation
Category: otc | Type: HUMAN OTC DRUG LABEL
Date: 20250908

ACTIVE INGREDIENTS: CALCIUM CARBONATE 750 mg/1 1
INACTIVE INGREDIENTS: DEXTROSE; FD&C BLUE NO. 1; FD&C RED NO. 40; MAGNESIUM STEARATE; MALTODEXTRIN

Green Guard Maximum Strength Stomach Relief

Drug Facts

Active ingredient (in each tablet)

Calcium Carbonate USP 750 mg

Purpose

Antacid

Uses

relieves

- acid indigestion
- sour stomach
- heartburn
- upset stomach associated with these symptoms

Warnings

Do not use

- the maximum dosage of this product for more than 2 weeks except under the advice and supervision of a doctor

Ask a doctor or pharmacist before use if you

- are taking a preceription drug. Antacids may interact with certain prescription drugs.
- have kidney disease

When using this product

- do not take more than 10 tablets in 24 hours
- if pregnant, do not take more than 6 tablets in 24 hours

Keep out of reach of children.

Directions

- do not take for symptoms that persisit for more than 2 weeks unless advised by a doctor

Adults and children: (12 years and over) Chew 2 to 4 tablets as symptoms occur or as directed by a doctor

Children under 12 years: Ask a doctor

Other information

- calcium content per tablet: 300 mg
- 5 calories per tablet
- store at room temperature 59-86ºF (15-30ºC) in a dry place
- tamper-evident sealed packets
- do not use any opened or torn packets

Inactive ingredients

assorted flavors, dextrose, FD&C blue #1 aluminum lake, FD&C red #40 aluminum lake, magnesium stearate, maltodextrin

Questions or comments? Call 1-800-869-6970

Green Guard Maximum Strength Stomach Relief Label

Maximum Strength

Stomach relief™

Pull to Open

Tire Para Abrir

Calcium Carbonate 750 mg

Carbonato de Calcio 750 mg

Heartburn, Indigestion

las agruras, la indigestion

Assorted Berry

Bayas surtidas

Green Guard®

50 Packets of 2 Tablets

100 Tablets

Order #2280

Distributed by Green Guard ®

St Louis, MO 63045